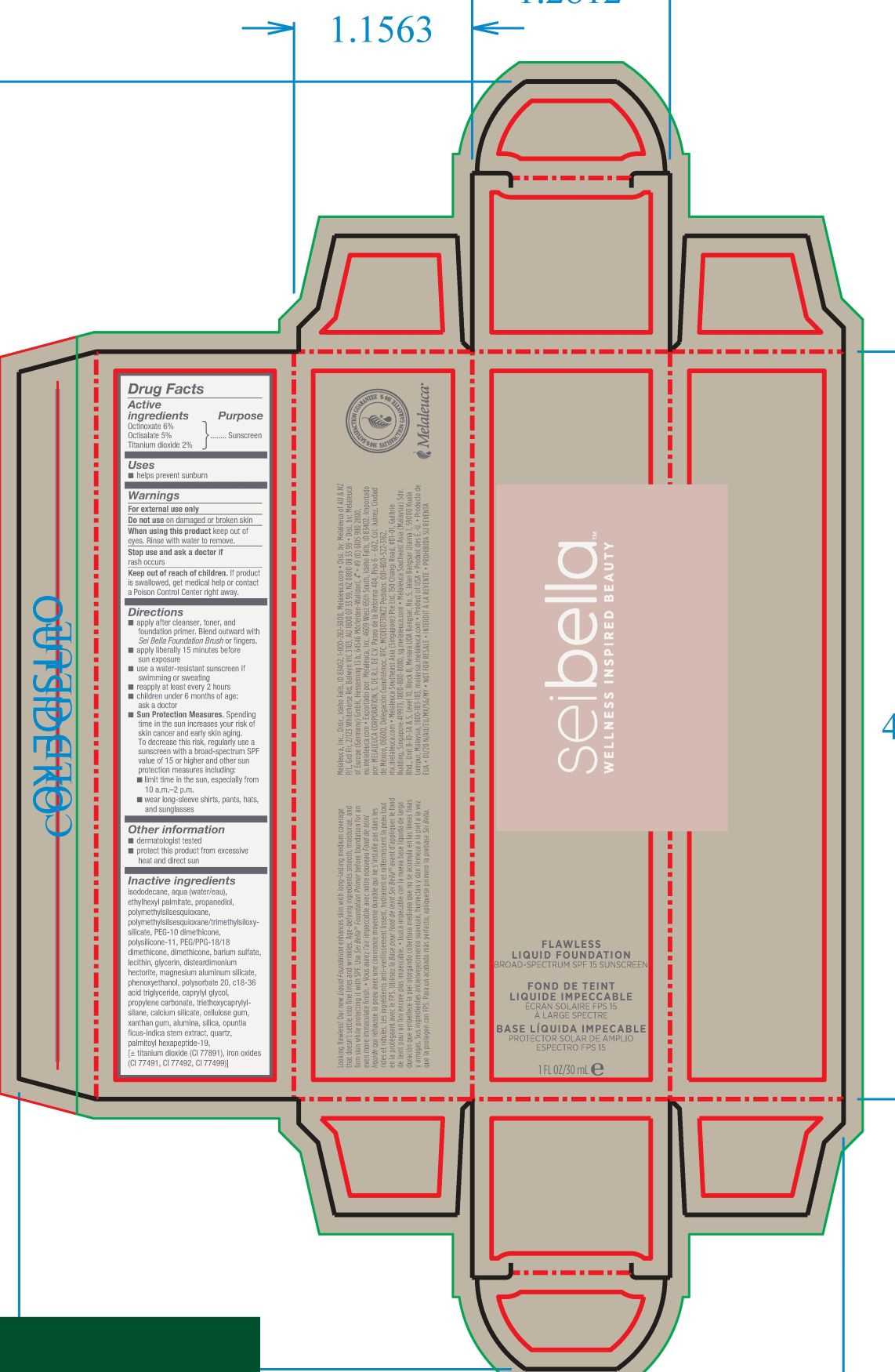 DRUG LABEL: Sei Bella Flawless Liquid Foundation
NDC: 54473-316 | Form: LOTION
Manufacturer: Melaleuca Inc.
Category: otc | Type: HUMAN OTC DRUG LABEL
Date: 20230111

ACTIVE INGREDIENTS: OCTISALATE 1.5 g/30 mL; OCTINOXATE 1.8 g/30 mL; TITANIUM DIOXIDE 0.6 g/30 mL
INACTIVE INGREDIENTS: FERRIC OXIDE YELLOW; POLYSORBATE 20; TRIETHOXYCAPRYLYLSILANE; ISODODECANE; PHENOXYETHANOL; C18-36 ACID TRIGLYCERIDE; CARBOXYMETHYLCELLULOSE SODIUM; OPUNTIA FICUS-INDICA STEM; SILICON DIOXIDE; WATER; XANTHAN GUM; CAPRYLYL GLYCOL; GLYCERIN; LECITHIN, SOYBEAN; POLYMETHYLSILSESQUIOXANE (4.5 MICRONS); DISTEARDIMONIUM HECTORITE; MAGNESIUM ALUMINUM SILICATE; PROPYLENE CARBONATE; CALCIUM SILICATE; PALMITOYL HEXAPEPTIDE-12; FERRIC OXIDE RED; FERROSOFERRIC OXIDE; DODECANE; ETHYLHEXYL PALMITATE; PROPANEDIOL; TRIMETHYLSILOXYSILICATE (M/Q 0.66); PEG-10 DIMETHICONE (600 CST); POLYSILICONE-15; PEG/PPG-18/18 DIMETHICONE; DIMETHICONE; BARIUM SULFATE

Sei Bella Flawless Liquid Foundation - 280 N

Active Ingredient

Octinoxate 7.5%

Purpose

Sunscreen

Use

■ helps prevent sunburn

Warnings

For external use only

Do not use on damaged or broken skin

When using this product keep out of eyes. Rinse with water to remove.

Stop use and ask a doctor if rash occurs

Keep out of reach of children.

If swallowed, get medical help or contact a Poison Control Center right away.

Directions

■ apply after cleanser, toner, and foundation primer. Blend outward with Sei Bella foundation brush or fingers.

■ apply liberally 15 minutes before sun exposure

■ use a water-resistant sunscreen if swimming or sweating

■ reapply at least every 2 hours

■ children under 6 months: ask a doctor

■ Sun Protection Measures. Spending time in the sun increases you risk of skin cancer and early skin aging. To decrease this risk, regularly use a sunscreen with a broad-spectrum SPF value of 15 or higher and other sun protection measures including:

■ limit time in the sun, especially from 10 a.m.-2 p.m.

■ wear long-sleeve shirts, pants, hats, and sunglasses

Other information

■ dermatologist and allergy tested

STORAGE AND HANDLING

■ protect this product from excesssive heat and direct sun

Inactive ingredients

isododecane, water, titanium oxide, dodecane, ethylhexyl palmitate, propanediol, polymethylsilsesquioxane, trimethylsiloxysilicate, peg-10 dimethicone, polysilicone-11, peg/ppg-18/18 dimethicone, dimethicone, barium sulfate, lecithin, glycerin, disteardimonium hectorite, magnesium aluminum silicate, phenoxyethanol, polysorbate 20, c18-36 acid triglyceride, caprylyl glycol, propylene carbonate, triethoxycaprylylsilane, calcium silicate, xanthum gum, cellulose gum, ouptnia ficus-indica stem extract, quartz, palmitoyl hexapeptide-19, may contain: iron oxide CI 77492, iron oxide 77491, iron oxide 77499